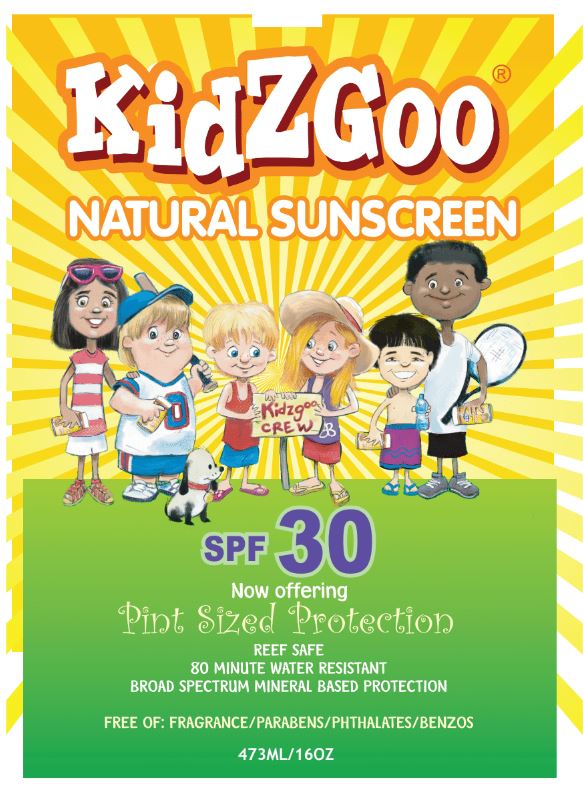 DRUG LABEL: KidZGoo Natural Sunscreen
NDC: 76348-650 | Form: LOTION
Manufacturer: RENU LABORATORIES, INC.
Category: otc | Type: HUMAN OTC DRUG LABEL
Date: 20210804

ACTIVE INGREDIENTS: ZINC OXIDE 98.56 g/448 g
INACTIVE INGREDIENTS: STYRENE/ACRYLAMIDE COPOLYMER (MW 500000); PANTHENOL; SILICON DIOXIDE; WATER; PHENOXYETHANOL; CETOSTEARYL ALCOHOL; PHYTATE SODIUM; XANTHAN GUM; ALPHA-TOCOPHEROL ACETATE; POLYHYDROXYSTEARIC ACID (2300 MW); CETEARYL OLIVATE; STEARYL/OCTYLDODECYL CITRATE CROSSPOLYMER; CAPRYLYL GLYCOL; SORBITAN OLIVATE; COCO-CAPRYLATE

KidZGoo Natural Sunscreen

Active Ingredient

Zinc Oxide

Purpose

Sunscreen

Warnings

- For external use only
- Do not use on damaged or broken skin
- When using this product, keep out of eyes. Rinse with water to remove.
- Stop use and ask a doctor if rash occurs
- Keep out of reach of children. If swallowed, get medical help or contact a Poison Control Center right away.

Stop use and ask a doctor if rash occurs

Do not use on damaged or broken skin

Keep out of reach of children. If swallowed, get medical help or contact a Poison Control Center right away.

QUESTIONS

855-KIDZGOO

Melearning Media LLC

Upper Dublin, PA

Directions

- apply liberally 15 minutes before sun exposure
- reapply;
  - after 80 minutes of swimming or sweating
  - immediately after towel drying
  - at least every 2 hours

OTHER SAFETY INFORMATION

Sun Protection Measures.

Spending time in the sun increases your risk of skin cancer and early skin aging. To decrease this risk, regularly use a sunscreen with a broad spectrum value of SPF 15 or higher and other sun protection measures including

- limit time in the sun, especially from 10 a.m. - 2 p.m.
- wear long-sleeved shirts, pants, hats, and sunglasses
- children under 6 months of age: Ask a doctor

Uses

- helps prevent sunburn if used as directed with other sun protection measures
- (see Directions)
- Decreases the risk of skin cancer and early skin aging caused by the sun.

Inactive Ingredients:

Benzyl Alcohol, Caprylic/Capric Triglyceride, Cetearyl Alcohol, Cetearyl Olivate, Coco-Caprylate, Dehydroacetic Acid, Deionized Water, Isostearic Acid, Lecithin, Microcrystalline Cellulose, Panthenol, Polyglyceryl-3, Polyhydroxystearic Acid, Silica, Sodium Phytate, Sorbitan Olivate, Stearyl Octyldodecyl Citrate Crosspolymer, Tocopherol, Xantan Gum